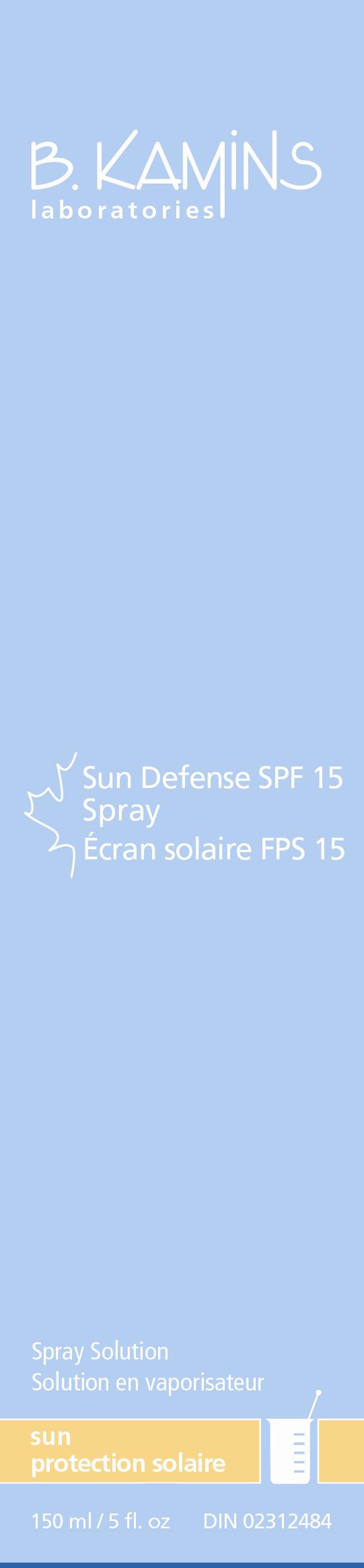 DRUG LABEL: SUN DEFENSE SPF 15
NDC: 63550-850 | Form: SPRAY
Manufacturer: Kamins Dermatologics Inc.
Category: otc | Type: HUMAN OTC DRUG LABEL
Date: 20110902

ACTIVE INGREDIENTS: AVOBENZONE 30 mg/1 mL; HOMOSALATE 100 mg/1 mL; OCTISALATE 50 mg/1 mL; OXYBENZONE 60 mg/1 mL
INACTIVE INGREDIENTS: MALIC ACID; DIETHYLHEXYL 2,6-NAPHTHALATE; PPG-5-CETETH-20; ETHYLENE BRASSYLATE; .ALPHA.-TOCOPHEROL ACETATE, D-; ACER SACCHARUM SAP; POMEGRANATE; PROPYLENE GLYCOL; WATER; ACAI; VITAMIN A PALMITATE; MAGNESIUM ASCORBYL PHOSPHATE; ALCOHOL

SUN DEFENSE SPF15 - CONSUMER LABELING

Active ingredients:

Avobenzone 3%

Homosalate 10%

Octisalate 5%

Oxybenzone 6%

Purpose: Sunscreen

Keep out of reach of children.

INDICATIONS AND USAGE

A broad spectrum UVA/UVB sunscreen to help protect the skin from sunburn. Sun Defense Spray SPF 15 is enriched with moisturizing açai oil, pomegranate extract and Bio-MapleTM compound to help skin remain hydrated.

Uses
■ Helps prevent sunburn.

■ Higher SPF gives more sunburn protection.

■ Provides high protection against sunburn.

Warnings
For external use only.
When using this product, keep out of eyes. If contact occurs, rinse abundantly with water to remove.
Stop use and ask a doctor if rash or irritation develops and lasts.
If swallowed, seek medical assistance or contact a Poison Control Center immediately.

Flammable: Keep away from open flame or source of heat. Do not use while smoking. Avoid long term storage above 40 °C (104°F)

Other information

Sun alert: Limiting sun exposure, wearing protective clothing, and using sunscreens may reduce the risks of skin aging, skin cancer, and other harmful effects of the sun.

Directions

■ Apply 15-30 minutes before sun exposure.
■ Hold bottle 8-10 inches from the skin and press pump to spray a fine even mist.

■ Spray liberally and evenly over all exposed areas to ensure complete coverage.

■ Do not spray directly onto face; spray into hands, then immediately apply to face.

■ Rub into skin on all exposed areas.

■ Reapply every two hours or as needed, after swimming, washing, towel drying, or perspiring heavily.

INACTIVE INGREDIENT

Inactive ingredients: alcohol denat., ethyl macadamiate, tocopherol, malic acid, diethylhexyl 2,6-naphthalate, PPG-5-ceteth-20, acrylates/octylacrylamide copolymer, ethylene brassylate, lauryl PCA, tocopheryl acetate, acer saccharum (maple isolate), punica granatum (pomegranate) extract, propylene glycol, water, euterpe oleracea (acai) oil, retinyl palmitate, magnesium ascorbyl phosphate.

PACKAGE LABEL

B. KAMINS

SUN DEFENSE SPRAY SPF15

150mL / 5 fl.oz

DIN 02312484

image/jpg